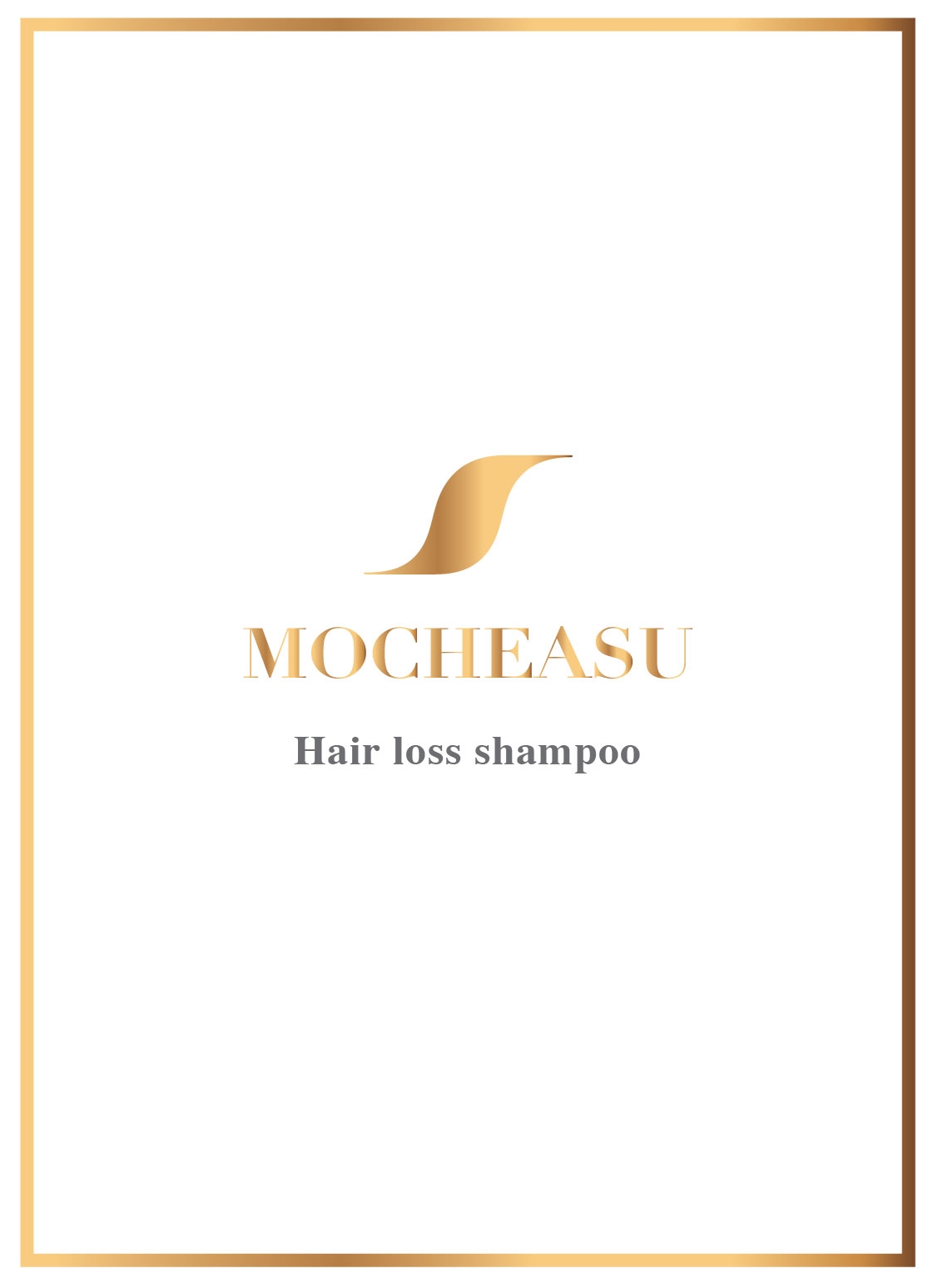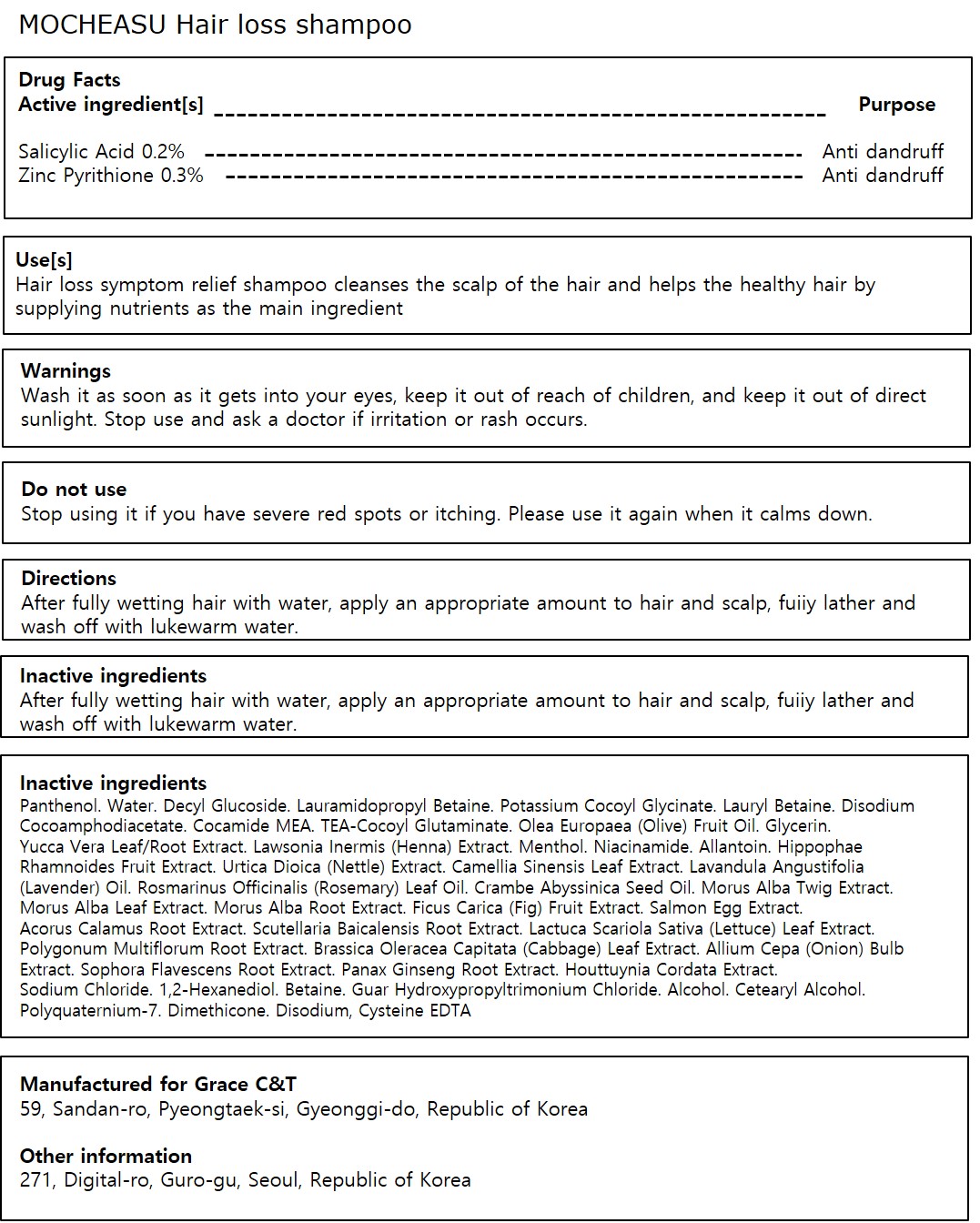 DRUG LABEL: MOCHEASU ALOPECIA-Shampoo
NDC: 79546-201 | Form: SHAMPOO
Manufacturer: Somi T Na Co., Ltd
Category: otc | Type: HUMAN OTC DRUG LABEL
Date: 20230516

ACTIVE INGREDIENTS: PYRITHIONE ZINC 0.3 g/100 mL; SALICYLIC ACID 0.2 g/100 mL
INACTIVE INGREDIENTS: POTASSIUM COCOYL GLYCINATE; OLIVE OIL; PANTHENOL; DECYL GLUCOSIDE; CYSTEINE; SOPHORA FLAVESCENS ROOT; ASIAN GINSENG; MORUS ALBA STEM; SALMON, UNSPECIFIED; ACORUS CALAMUS ROOT; SCUTELLARIA BAICALENSIS ROOT; LETTUCE; REYNOUTRIA MULTIFLORA ROOT; ONION; HOUTTUYNIA CORDATA FLOWERING TOP; SODIUM CHLORIDE; BETAINE; ALCOHOL; DIMETHICONE; LAURYL BETAINE; TRIETHANOLAMINE COCOYL GLUTAMINATE; LAWSONIA INERMIS FLOWERING TOP; MENTHOL; NIACINAMIDE; ALLANTOIN; URTICA DIOICA LEAF; 1,2-HEXANEDIOL; EDETATE DISODIUM ANHYDROUS; GUAR HYDROXYPROPYLTRIMONIUM CHLORIDE (1.7 SUBSTITUENTS PER SACCHARIDE); CETOSTEARYL ALCOHOL; POLYQUATERNIUM-7 (70/30 ACRYLAMIDE/DADMAC; 1600000 MW); COCO MONOETHANOLAMIDE; YUCCA SCHIDIGERA; LAURAMIDOPROPYL BETAINE; DISODIUM COCOAMPHODIACETATE; GLYCERIN; GREEN TEA LEAF; ROSEMARY OIL; CABBAGE; WATER; HIPPOPHAE RHAMNOIDES FRUIT; LAVENDER OIL; CRAMBE HISPANICA SUBSP. ABYSSINICA SEED OIL; MORUS ALBA LEAF; MORUS ALBA ROOT; FIG

Active ingredient

Salicylic Acid 0.2%

Zinc Pyrithione 0.3%

Purpose

Anti dandruff

Use

Hair loss symptom relief shampoo cleanses the scalp of the hair and helps the healthy hair by supplying nutrients as the main ingredient

Warnings

Wash it as soon as it gets into your eyes

Warnings

keep it out of reach of children

Warnings

and keep it out of direct sunlight

Warnings

Stop use and ask a doctor if irritation or rash occurs.

Directions

After fully wetting hair with water, apply an appropriate amount to hair and scalp, fuiiy lather and wash off with lukewarm water.

Inactive ingredients

Water, Decyl Glucoside, Lauramidopropyl Betaine, Potassium Cocoyl Glycinate, Lauryl Betaine, Disodium Cocoamphodiacetate, Cocamide MEA, TEA-Cocoyl Glutaminate, Olea Europaea (Olive) Fruit Oil, Glycerin, Yucca Vera Leaf/Root Extract, Lawsonia Inermis (Henna) Extract, Menthol, Niacinamide, Allantoin, Hippophae Rhamnoides Fruit Extract, Urtica Dioica (Nettle) Extract, Camellia Sinensis Leaf Extract, Lavandula Angustifolia (Lavender) Oil, Rosmarinus Officinalis (Rosemary) Leaf Oil, Crambe Abyssinica Seed Oil, Morus Alba Twig Extract, Morus Alba Leaf Extract, Morus Alba Root Extract, Ficus Carica (Fig) Fruit Extract, Salmon Egg Extract, Acorus Calamus Root Extract, Scutellaria Baicalensis Root Extract, Cysteine, Lactuca Scariola Sativa (Lettuce) Leaf Extract, Polygonum Multiflorum Root Extract, Brassica Oleracea Capitata (Cabbage) Leaf Extract, Allium Cepa (Onion) Bulb Extract, Sophora Flavescens Root Extract, Panax Ginseng Root Extract, Houttuynia Cordata Extract, Sodium Chloride, 1,2-Hexanediol, Betaine, Guar Hydroxypropyltrimonium Chloride, Alcohol, Cetearyl Alcohol, Polyquaternium-7, Dimethicone, Disodium EDTA